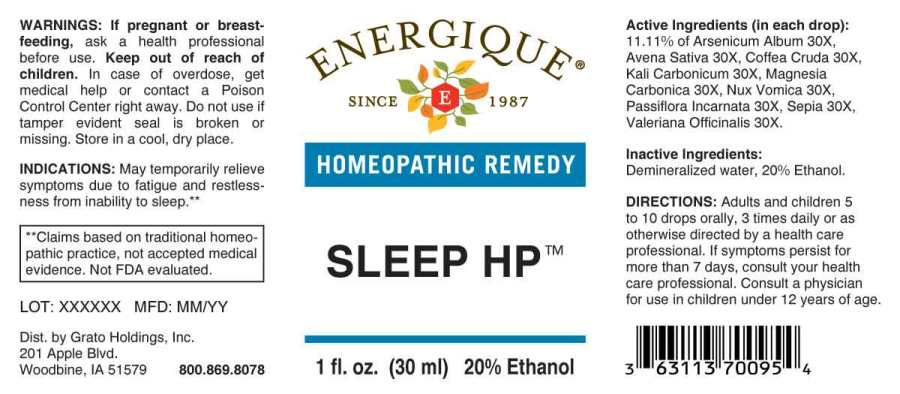 DRUG LABEL: Sleep HP
NDC: 70163-0002 | Form: LIQUID
Manufacturer: Grato Holdings, Inc.
Category: homeopathic | Type: HUMAN OTC DRUG LABEL
Date: 20201130

ACTIVE INGREDIENTS: ARSENIC TRIOXIDE 30 [hp_X]/1 mL; AVENA SATIVA FLOWERING TOP 30 [hp_X]/1 mL; ARABICA COFFEE BEAN 30 [hp_X]/1 mL; POTASSIUM CARBONATE 30 1/1 mL; MAGNESIUM CARBONATE 30 [hp_X]/1 mL; STRYCHNOS NUX-VOMICA SEED 30 [hp_X]/1 mL; PASSIFLORA INCARNATA FLOWERING TOP 30 [hp_X]/1 mL; SEPIA OFFICINALIS JUICE 30 [hp_X]/1 mL; VALERIAN 30 [hp_X]/1 mL
INACTIVE INGREDIENTS: WATER; ALCOHOL

Drug Facts:

ACTIVE INGREDIENTS:

(in each drop): 11.11% of Arsenicum Album 30X, Avena Sativa 30X, Coffea Cruda 30X, Kali Carbonicum 30X, Magnesia Carbonica 30X, Nux Vomica 30X, Passiflora Incarnata 30X, Sepia 30X, Valeriana Officinalis 30X.

INDICATIONS:

May temporary relieve symptoms due to fatigue and restlessness from inability to sleep.**

**Claims based on traditional homeopathic practice. Not FDA evaluated.

WARNINGS:

If pregnant or breast-feeding, ask a health professional before use.

Keep out of reach of children. In case of overdose, get medical help or contact a Poison Control Center right away.

Do not use if tamper evident seal is broken or missing. Store in a cool, dry place.

Keep out of reach of children. In case of overdose, get medical help or contact a Poison Control Center right away.

DIRECTIONS:

Adults and children 5 to 10 drops orally, 3 times daily or as otherwise directed by a health care professional. If symptoms persist for more than 7 days, consult your health care professional. Consult a physician for use in children under 12 years of age.

INDICATIONS:

May temporary relieve symptoms due to fatigue and restlessness from inability to sleep.**

**Claims based on traditional homeopathic practice, not accepted medical evidence. Not FDA evaluated.

INACTIVE INGREDIENTS:

Demineralized water, 20% Ethanol.

QUESTIONS:

Dist. by Grato Holdings, Inc.

201 Apple Blvd.

Woodbine, IA 51579 800-869-8078

PACKAGE LABEL DISPLAY:

ENERGIQUE

SINCE 1987

HOMEOPATHIC REMEDY

SLEEP HP

1 fl. oz. (30 ml)